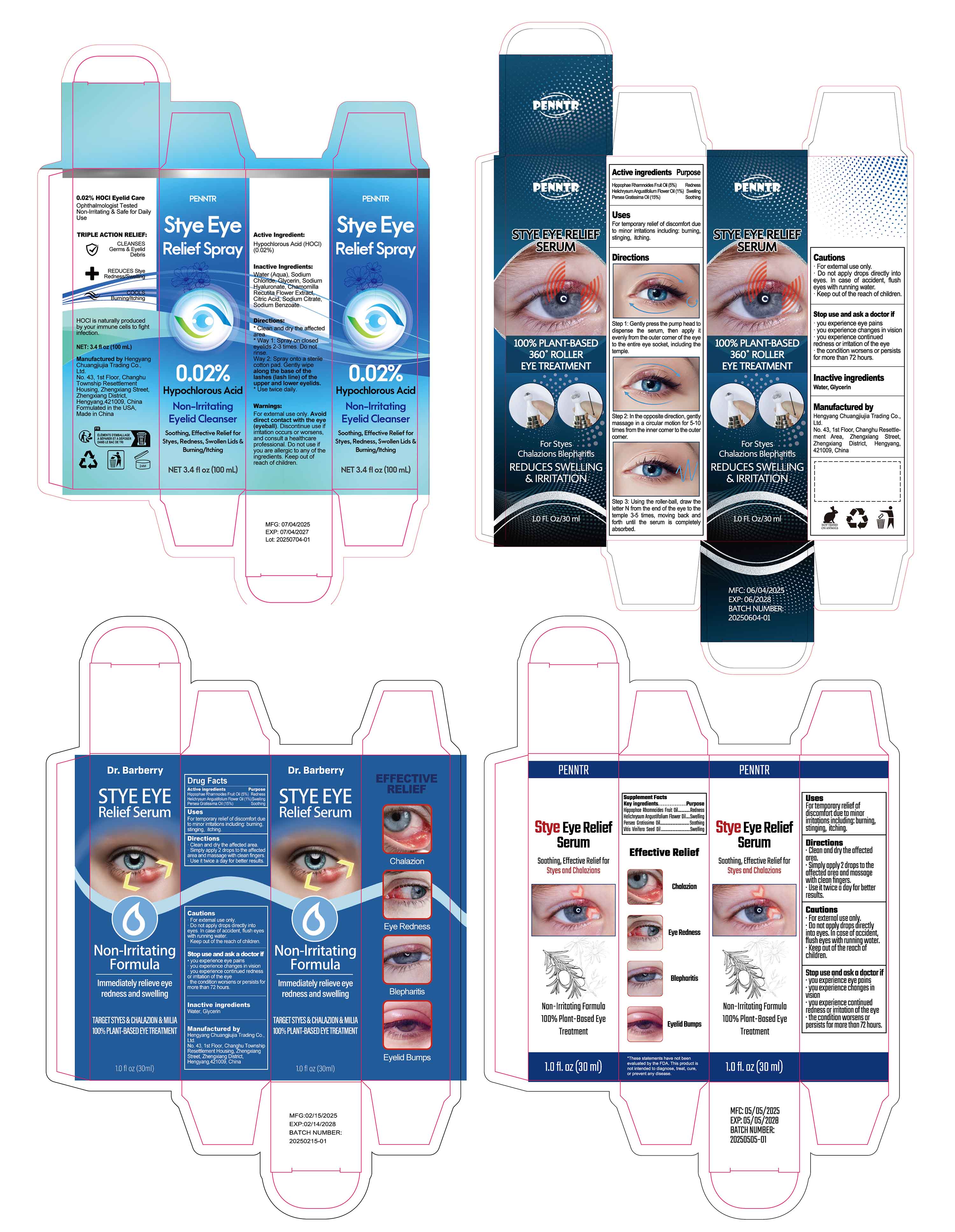 DRUG LABEL: Stye Eye Relief Serum
NDC: 84735-011 | Form: LIQUID
Manufacturer: Hengyang Chuangjiujia Trading Co., Ltd.
Category: otc | Type: HUMAN OTC DRUG LABEL
Date: 20250716

ACTIVE INGREDIENTS: HIPPOPHAE RHAMNOIDES FRUIT OIL 1.5 g/30 mL; HELICHRYSUM ANGUSTIFOLIUM FLOWER OIL 0.3 g/30 mL; PERSEA GRATISSIMA (AVOCADO) OIL 4.5 g/30 mL
INACTIVE INGREDIENTS: GLYCERIN; WATER

84735-011 Stye Eye Relief Serum

ACTIVE INGREDIENT

Hippophae Rhamnoides Fruit Oil 5%
Helichrysum Angustifolium Flower Oil 1%
Persea Gratissima Oil 15%

PURPOSE

Redness, Swelling, Soothing

INDICATIONS AND USAGE

For temporary relief of discomfort dueto minor irritations including: burningstinging, itching

WARNINGS

For extemal use only.
Do not apply drops directly intoeyes. In case of accident, flush eyeswith running water.
Keep out of the reach of children.

DO NOT USE

Do not apply drops directly intoeyes. In case of accident, flush eyeswith running water.

STOP USE

you experlence eye pains
you experience changes in vision
you experience continued rednessor irritation of the eye
the condition worsens or persists formore than 72 hours

Keep out of the reach of children.

DOSAGE AND ADMINISTRATION

Clean and dry the affected area.
Simply apply 2 drops to the affectedarea and massage with clean fingers.
Use it twice a day for better results.

INACTIVE INGREDIENT

WATER
GLYCERIN